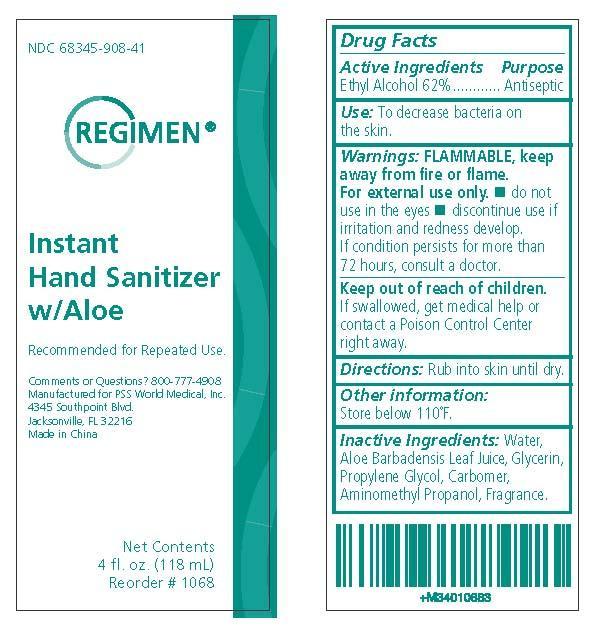 DRUG LABEL: Regimen
NDC: 68345-908 | Form: GEL
Manufacturer: PSS World Medical, Inc.
Category: otc | Type: HUMAN OTC DRUG LABEL
Date: 20120905

ACTIVE INGREDIENTS: ALCOHOL 62 mL/100 mL
INACTIVE INGREDIENTS: Water; Aloe Vera Leaf; Glycerin; Propylene Glycol; Carbomer Homopolymer Type C; AminomethylPropanol

Drug Facts

Active Ingredient

Ethyl Alcohol 62%

Purpose

Antiseptic

Use

To decrease bacteria on the skin.

Recommended for Repeated Use.

Warnings

FLAMMABLE, keep away from fire or flame. For external use only.

Do not use in the eyes. Discontinue use if irritation and redness develop.

Stop Use and Ask Doctor If

If condition persists for more than 72 hours, consult a doctor.

Keep Out of Reach of Children

If swallowed, get medical help or contact a Poison Control Center right away.

Directions

Pump as needed into hands and rub thoroughly into the skin until dry.

Other Information

Store below 110°F.

Inactive Ingredients

Water, Aloe Barbadensis Leaf Juice, Glycerin, Propylene Glycol, Carbomer, Aminomethyl Propanol, Fragrance.

Questions

Comments or Questions? 800-777-4908

Manufactured for PSS World Medical, Inc.
4345 Southpoint Blvd.
Jacksonville, FL 32216
Made in China

PACKAGE LABEL

Principal Display Panel
NDC 68345-908-41